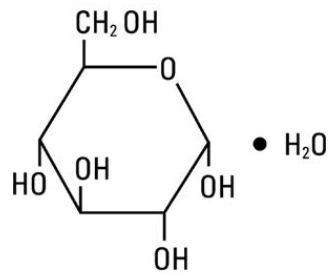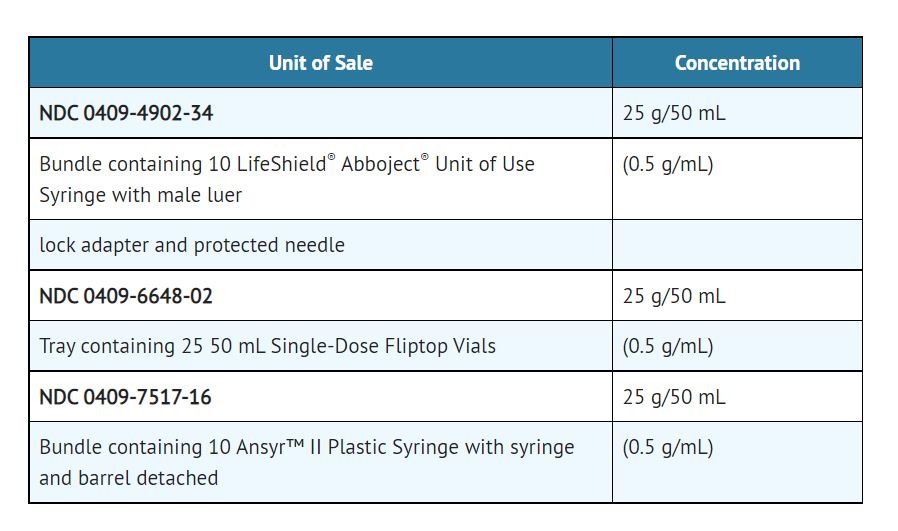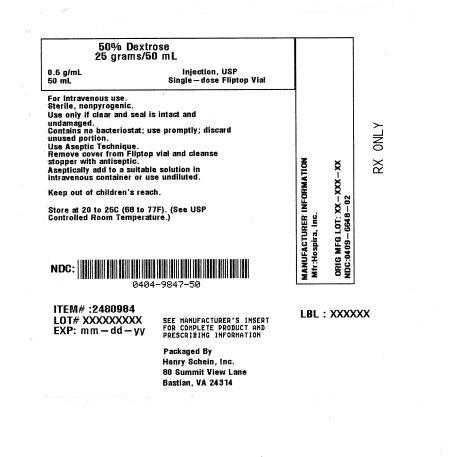 DRUG LABEL: Dextrose
								
NDC: 0404-9847 | Form: INJECTION, SOLUTION
Manufacturer: Henry Schein, Inc.
Category: prescription | Type: HUMAN PRESCRIPTION DRUG LABEL
Date: 20251003

ACTIVE INGREDIENTS: Dextrose Monohydrate 25 g/50 mL

Dextrose

Concentrated Dextrose for Intravenous Administration

NOTE: This solution is hypertonic - See WARNINGS and PRECAUTIONS.

LifeShield® Abboject® Syringe Fliptop Container

Ansyr™ II Plastic Syringe
Rx only

Descprition

50% Dextrose Injection, USP is a sterile, nonpyrogenic, hypertonic solution of dextrose in water for injection for intravenous injection as a fluid and nutrient replenisher.

Each mL of fluid contains 0.5 g dextrose, hydrous which delivers 3.4 kcal/gram. The solution has an osmolarity of 2.53 mOsmol/mL (calc.), a pH of 4.2 (3.2 to 6.5) and may contain sodium hydroxide and/or hydrochloric acid for pH adjustment.

The solution contains no bacteriostat, antimicrobial agent or added buffer (except for pH adjustment) and is intended only for use as a single-dose injection. When smaller doses are required, the unused portion should be discarded with the entire unit.

Dextrose, USP is chemically designated C6H12O6 ∙ H2O (D-glucose monohydrate), a hexose sugar freely soluble in water.

Dextrose, hydrous has the following structural formula:

Water for Injection, USP is chemically designated H2O.

The syringe is molded from a specially formulated polypropylene. Water permeates from inside the container at an extremely slow rate which will have an insignificant effect on solution concentration over the expected shelf life. Solutions in contact with the plastic container may leach out certain chemical components from the plastic in very small amounts; however, biological testing was supportive of the safety of the syringe material.

Clinical Pharmacolgy

When administered intravenously this solution restores blood glucose levels in hypoglycemia and provides a source of carbohydrate calories.

Carbohydrate in the form of dextrose may aid in minimizing liver glycogen depletion and exerts a protein-sparing action. Dextrose injection undergoes oxidation to carbon dioxide and water.

Water is an essential constituent of all body tissues and accounts for approximately 70% of total body weight. Average normal adult requirement ranges from two to three liters (1.0 to 1.5 liters each for insensible water loss by perspiration and urine production).

Water balance is maintained by various regulatory mechanisms. Water distribution depends primarily on the concentration of electrolytes in the body compartments and sodium (Na^+) plays a major role in maintaining physiologic equilibrium.

Indications and Usage

50% Dextrose Injection is indicated in the treatment of insulin hypoglycemia (hyperinsulinemia or insulin shock) to restore blood glucose levels.

The solution is also indicated, after dilution, for intravenous infusion as a source of carbohydrate calories in patients whose oral intake is restricted or inadequate to maintain nutritional requirements. Slow infusion of hypertonic solutions is essential to insure proper utilization of dextrose and avoid production of hyperglycemia.

Contraindications

A concentrated dextrose solution should not be used when intracranial or intraspinal hemorrhage is present, nor in the presence of delirium tremens if the patient is already dehydrated.

Dextrose injection without electrolytes should not be administered simultaneously with blood through the same infusion set because of the possibility that pseudoagglutination of red cells may occur.

Warnings

50% Dextrose Injection is hypertonic and may cause phlebitis and thrombosis at the site of injection.

Significant hyperglycemia and possible hyperosmolar syndrome may result from too rapid administration. The physician should be aware of the symptoms of hyperosmolar syndrome, such as mental confusion and loss of consciousness, especially in patients with chronic uremia and those with known carbohydrate intolerance.

The intravenous administration of this solution can cause fluid and/or solute overloading resulting in dilution of serum electrolyte concentrations, overhydration, congested states or pulmonary edema.

Additives may be incompatible. Consult with pharmacist if available. When introducing additives, use aseptic technique, mix thoroughly and do not store.

For peripheral vein administration:
The solution should be given slowly, preferably through a small bore needle into a large vein, to minimize venous irritation.

For central venous administration:
Concentrated dextrose should be administered via central vein only after suitable dilution.

Precautions

Do not use unless the solution is clear and seal is intact. Discard unused portion.

Electrolyte deficits, particularly in serum potassium and phosphate, may occur during prolonged use of concentrated dextrose solutions. Blood electrolyte monitoring is essential and fluid and electrolyte imbalances should be corrected. Essential vitamins and minerals also should be provided as needed.

To minimize hyperglycemia and consequent glycosuria, it is desirable to monitor blood and urine glucose and if necessary, add insulin.

When a concentrated dextrose infusion is abruptly withdrawn, it is advisable to follow with the administration of 5% or 10% dextrose injection to avoid rebound hypoglycemia.

Solutions containing dextrose should be used with caution in patients with known subclinical or overt diabetes mellitus.

Care should be exercised to insure that the needle is well within the lumen of the vein and that extravasation does not occur. If thrombosis should occur during administration, the injection should be stopped and corrective measures instituted.

Concentrated dextrose solutions should not be administered subcutaneously or intramuscularly.

Carcinogenesis, Mutagenesis, Impairment of Fertility

Studies with solutions in polypropylene syringes have not been performed to evaluate carcinogenic potential, mutagenic potential or effects on fertility.

Pregnancy: Animal reproduction studies have not been conducted with dextrose. It is also not known whether dextrose can cause fetal harm when administered to a pregnant woman or can affect reproduction capacity. Dextrose should be given to a pregnant woman only if clearly needed.

Nursing Mothers
It is not known whether this drug is excreted in human milk. Because many drugs are excreted in human milk, caution should be exercised when 50% Dextrose Injection, USP is administered to a nursing mother.

Adverse Reactions

Hyperosmolar syndrome, resulting from excessively rapid administration of concentrated dextrose may cause mental confusion and/or loss of consciousness.

Reactions which may occur because of the solution or the technique of administration include febrile response, infection at the site of injection, venous thrombosis or phlebitis extending from the site of injection, extravasation and hypervolemia.

If an adverse reaction does occur, discontinue the infusion, evaluate the patient, institute appropriate therapeutic countermeasures and save the remainder of the fluid for examination if deemed necessary.

Overdosage

In the event of overhydration or solute overload during therapy, re-evaluate the patient and institute appropriate corrective measures. See WARNINGS and PRECAUTIONS.

Dosage and Administration

For peripheral vein administration:

Injection of the solution should be made slowly.

The maximum rate at which dextrose can be infused without producing glycosuria is 0.5 g/kg of body weight/hour. About 95% of the dextrose is retained when infused ata rate of 0.8 g/kg/hr.

In insulin-induced hypoglycemia, intravenous injection of 10 to 25 grams of dextrose (20 to 50 mL of 50% dextrose) is usually adequate.Repeated doses and supportive treatment may be required in severe cases. A specimen for blood glucose determination should be taken before injecting the dextrose. In such emergencies, dextrose should be administered promptly without awaiting pretreatment test results.

For central venous administration:

For total parenteral nutrition 50% Dextrose Injection, USP is administered by slow intravenous infusion (a) after admixture with amino acid solutions via an indwelling catheter with the tip positioned in a large central vein, preferably the superior vena cava, or (b) after dilution with sterile water for injection. Dosage should be adjusted to meet individual patient requirements.

Clinical evaluation and periodic laboratory determinations are necessary to monitor changes in fluid balance, electrolyte concentrations and acid-base balance during prolonged parenteral therapy or whenever the condition of the patient warrants such evaluation.

The maximum rate of dextrose administration which does not result in glycosuria is the same as cited above.

Parenteral drug products should be inspected visually for particulate matter and discoloration prior to administration, whenever solution and container permit. See CONTRAINDICATIONS.

How Supplied

50% Dextrose Injection, USP is supplied in single-dose containers as follows:

Exposure of pharmaceutical products to heat should be minimized. Avoid excessive heat. Protect from freezing. Store at 20 to 25°C (68 to 77°F). [See USP Controlled Room Temperature.]

Abboject® is a trademark of Abbott Labaratories.

LifeShield® is the trademark of ICU Medical, Inc. and is used under license.

For Medical Information about 50% Dextrose Injection, please visit www.pfizermedinfo.com or call 1-800-438-1985

Product repackaged by: Henry Schein, Inc., Bastian, VA 24314
From Original Manufacturer/Distributor's NDC and Unit of Sale | To Henry Schein Repackaged Product NDC and Unit of Sale | Total Strength/Total Volume (Concentration) per unit
NDC 0409-6648-02 Tray containing 25 50 mL Single-Dose Fliptop Vials | NDC 0404-9847-50 1 Single-Dose Fliptop Vial per bag (Vial bears NDC 0409-6648-16) | 25 g/50 mL (0.5 g/mL)
NDC 0409-7517-16 Bundle containing 10 Ansyr™ II Plastic Syringe | NDC 0404-9845-50 1 Ansyr™ II Plastic Syringe per bag (Syringe bears NDC 0409-7517-66) | 25 g/50 mL (0.5mg/mL)

Distributedbb by Hospira, Inc., Lake Forest, IL 60045 USA

LAB-1027-5.0

Revised: February 2023